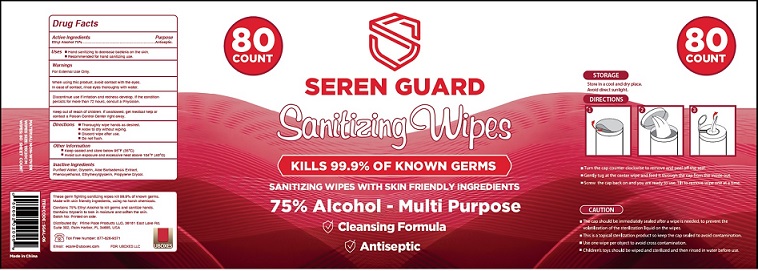 DRUG LABEL: SEREN GUARD
NDC: 79183-501 | Form: PATCH
Manufacturer: Prime Pace Products LLC
Category: otc | Type: HUMAN OTC DRUG LABEL
Date: 20201206

ACTIVE INGREDIENTS: ALCOHOL 75 g/100 g
INACTIVE INGREDIENTS: WATER; GLYCERIN; ALOE VERA FLOWER; PHENOXYETHANOL; ETHYLHEXYLGLYCERIN; PROPYLENE GLYCOL

SEREN GUARD Sanitizing Wipes

Drug Facts

Active Ingredients
Ethyl Alcohol 75%

Purpose
Antiseptic

INDICATIONS AND USAGE

Uses ■ Hand Sanitizer to decrease bacteria on skin.

■ Recommended for repeated use.

Warnings

For external use only.

When using this product keep out of eyes, ears, and mouth.
In case of contact with eyes, rinse eyes thoroughly with water.

STOP USE

Discontinue use if irritation and redness develop. If the condition
persists for more than 72 hours, consult a Physician.

Keep out of reach of children. If swallowed, get medical help or contact a Poison Control Center right away.

DOSAGE AND ADMINISTRATION

Directions ■ Thoroughly wipe hands as desired.
■ Allow to dry without wiping.
■ Discard wipe after use.
■ Do not flush.

Other Information

■ Keep sealed and store below 95°F (35°C)
■ Avoid sun exposure and excessive heat above 104°F (40°C)

Inactive ingredients

Purified Water, Glycerin, Aloe Barbadensis Extract,
Phenoxyethanol, Ethylhexylglycerin, Propylene Glycol.

Package Label - Principal Display Panel

80
COUNT

SEREN GUARD
Sanitizing Wipes

KILLS 99.9% OF KNOWN GERMS

SANITIZING WIPES WITH SKIN FRIENDLY INGREDIENTS

75% Alcohol - Multi Purpose

Cleansing Formula

Antiseptic

These germ fighting sanitizing wipes kill 99.9% of known germs.
Made with skin friendly ingredients, using no harsh chemicals.

Contains 75% Ethyl Alcohol to kill germs and sanitize hands.
Contains Glycerin to lock in moisture and soften the skin.
Batch No: Printed on side.

Distributed By: Prime Pace Products LLC, 36181 East Lake Rd,
Suite 302, Palm Harbor, FL 34685, USA

Toll Free Number: 877-826-9371

Email: ecare@uboxes.com

FOR: UBOXES LLC

MATERIAL: NON-WOVEN
WIPES SIZE: 15X20CM
WIPES: 80 SHEET COUNT

ITEM CODE : SGAL-06

0 5 0 6 6 2 0 2 0 0 6 9

Made in China

80 Wipes

res